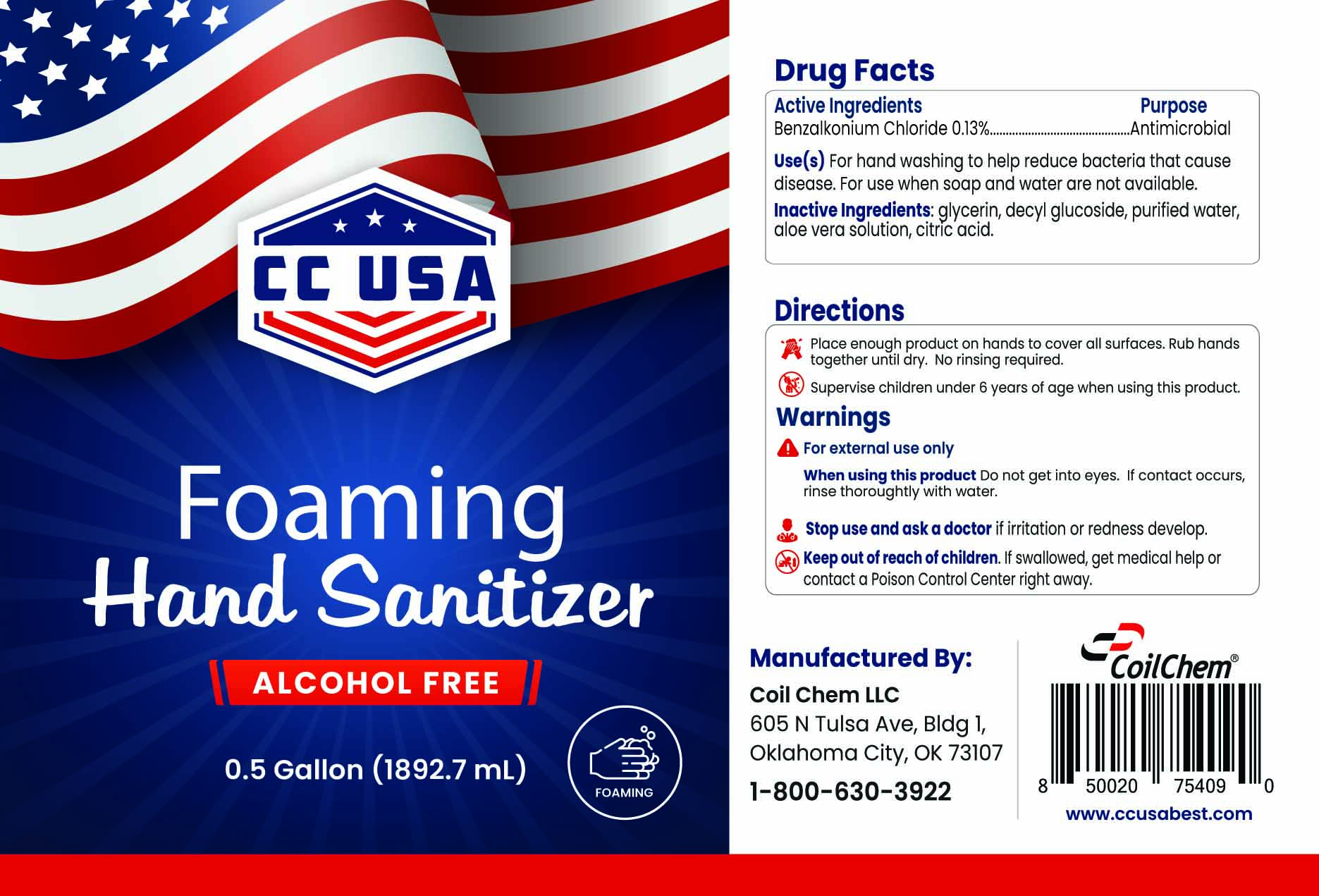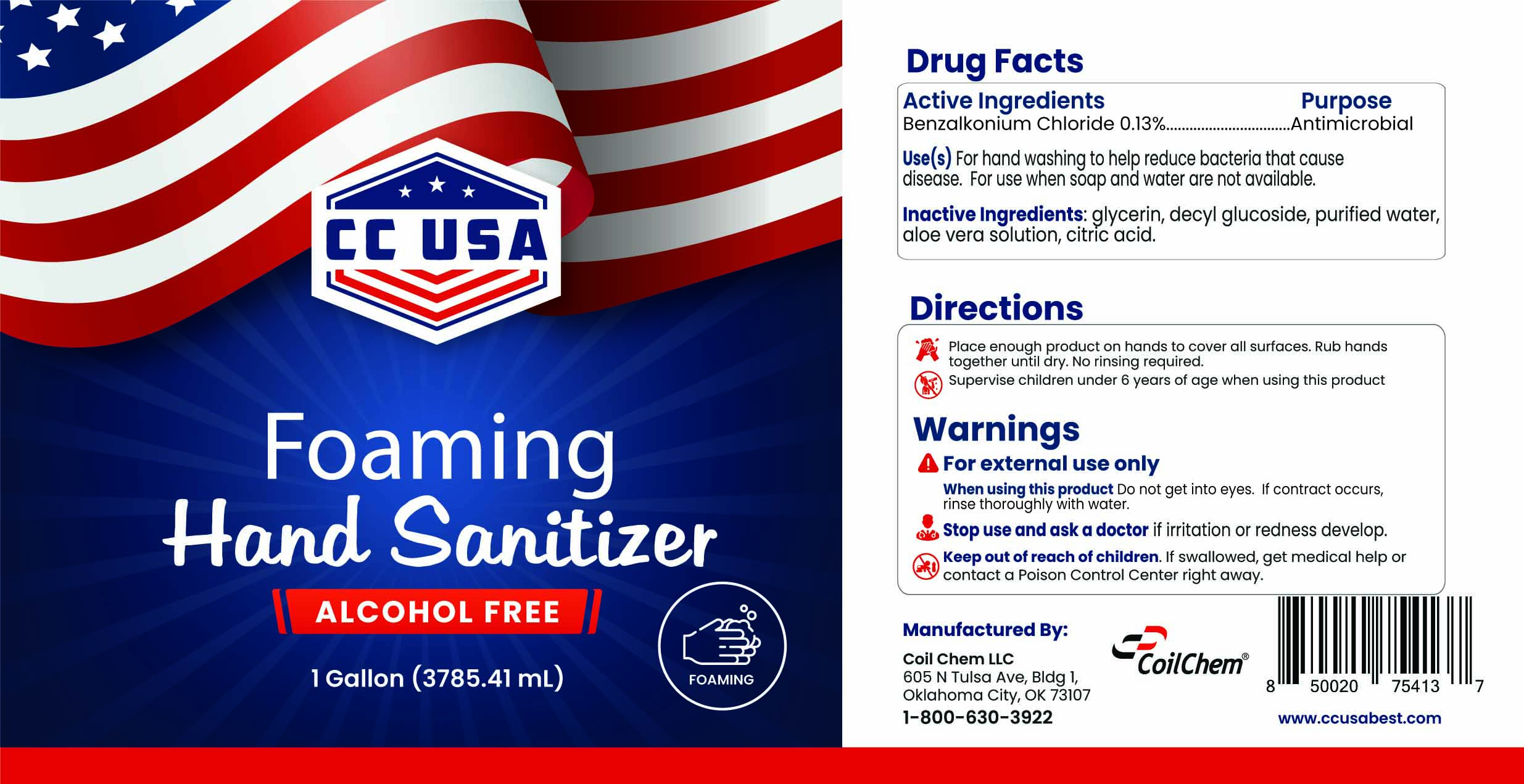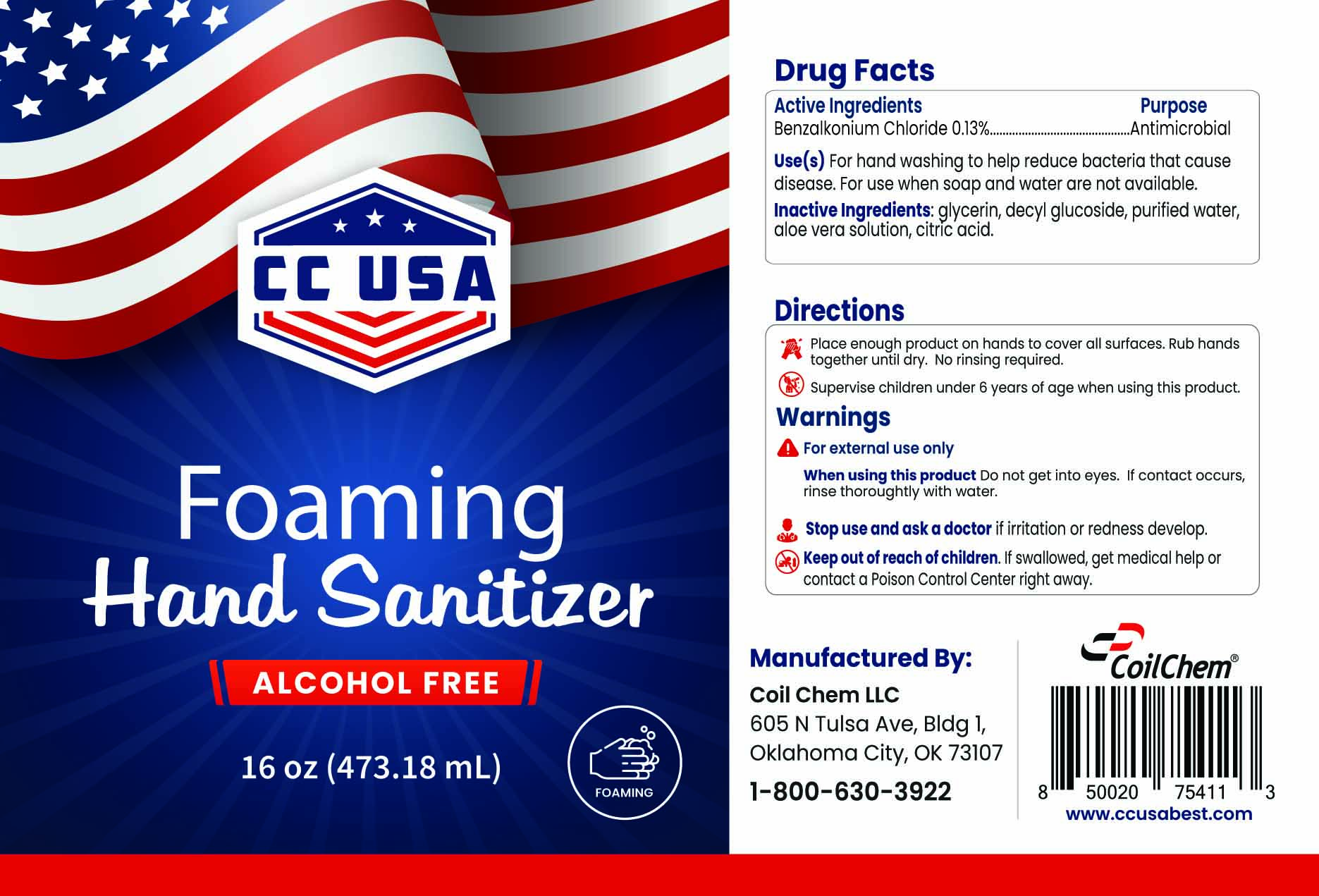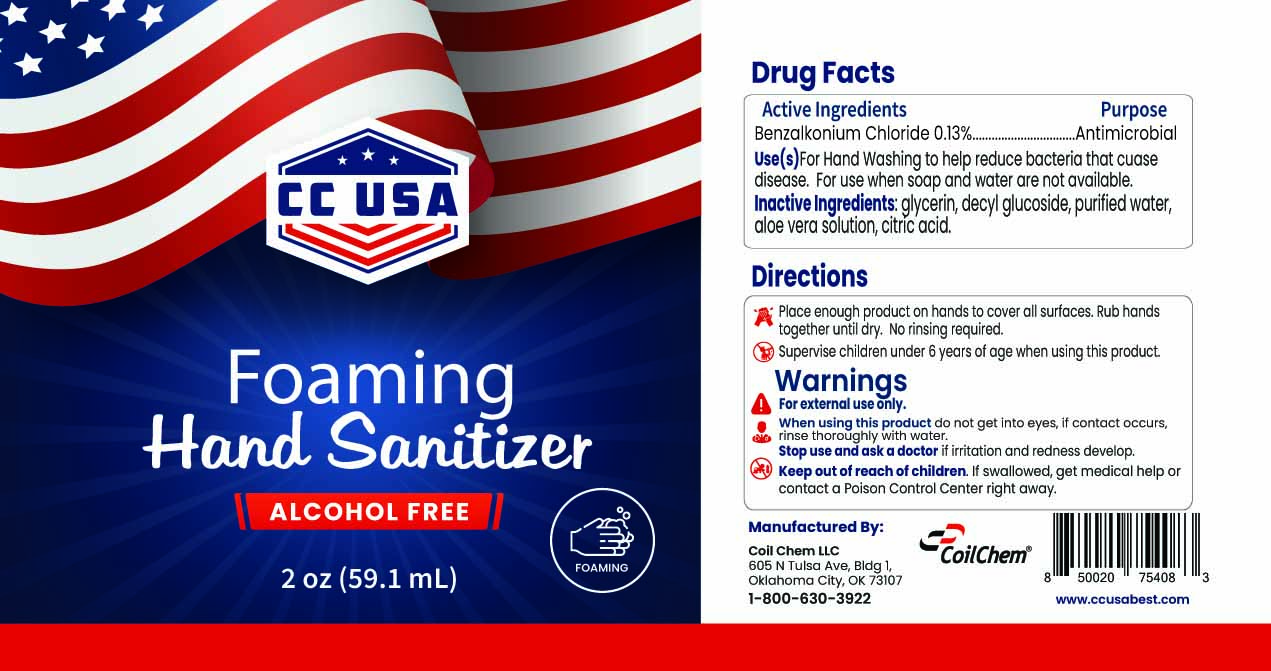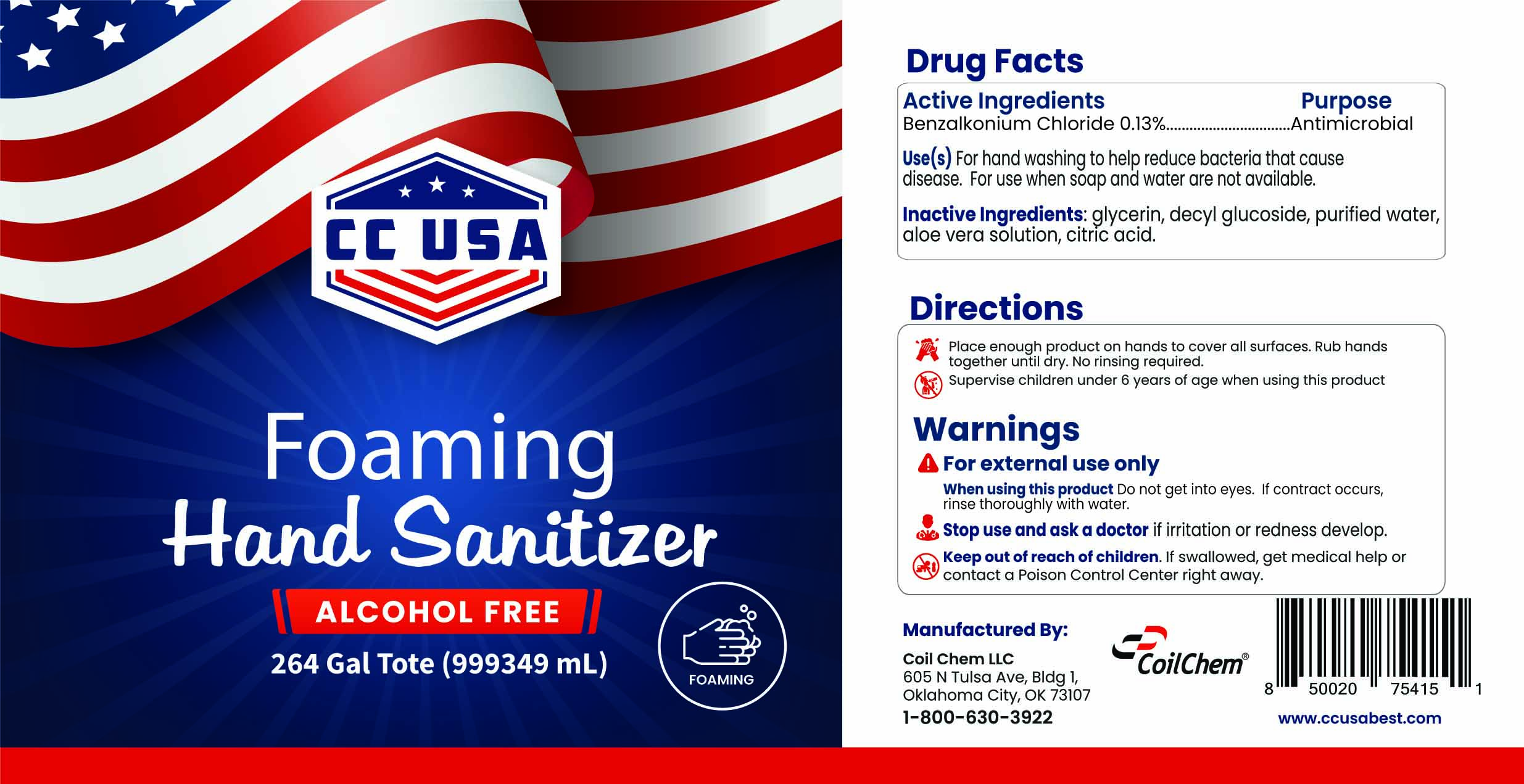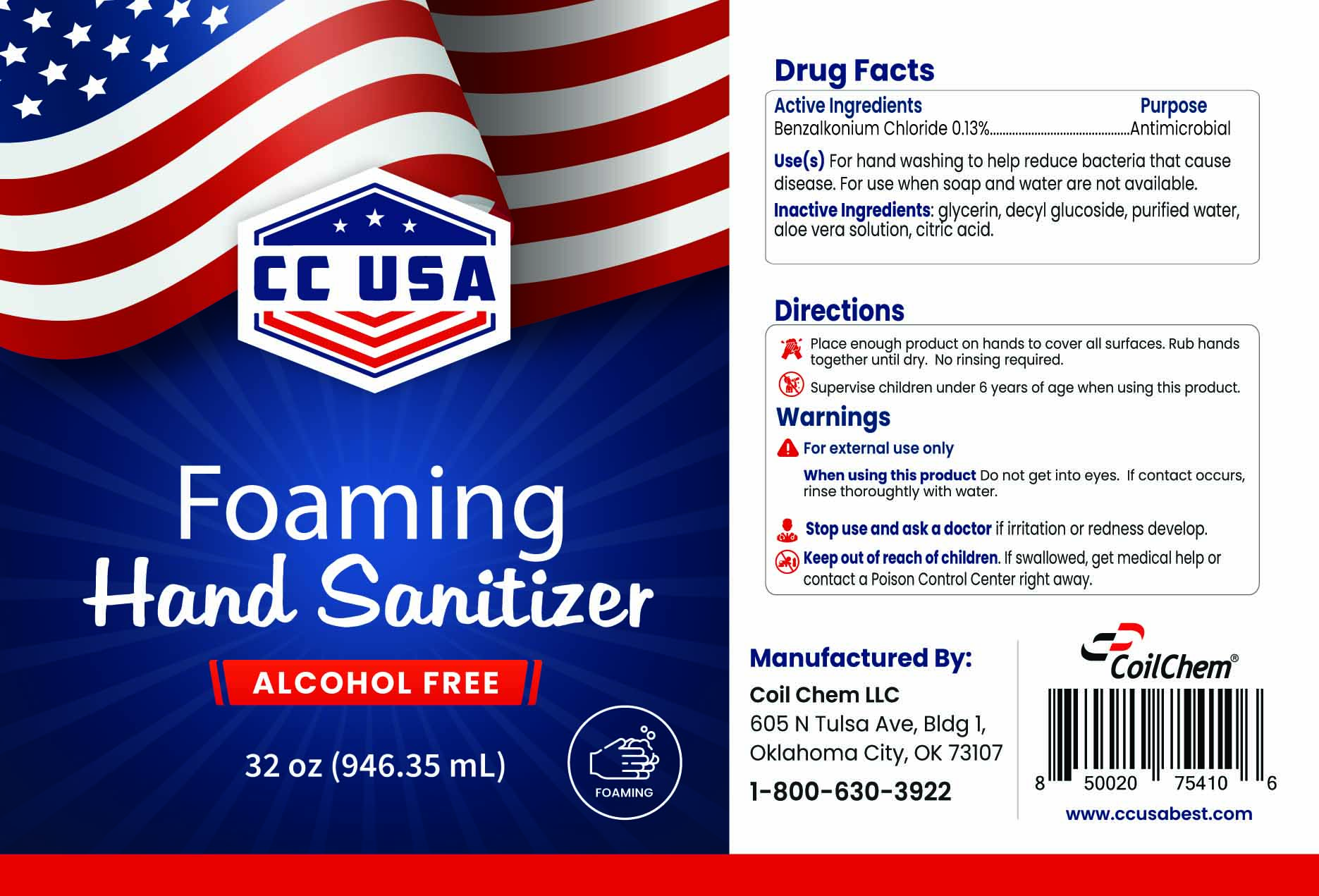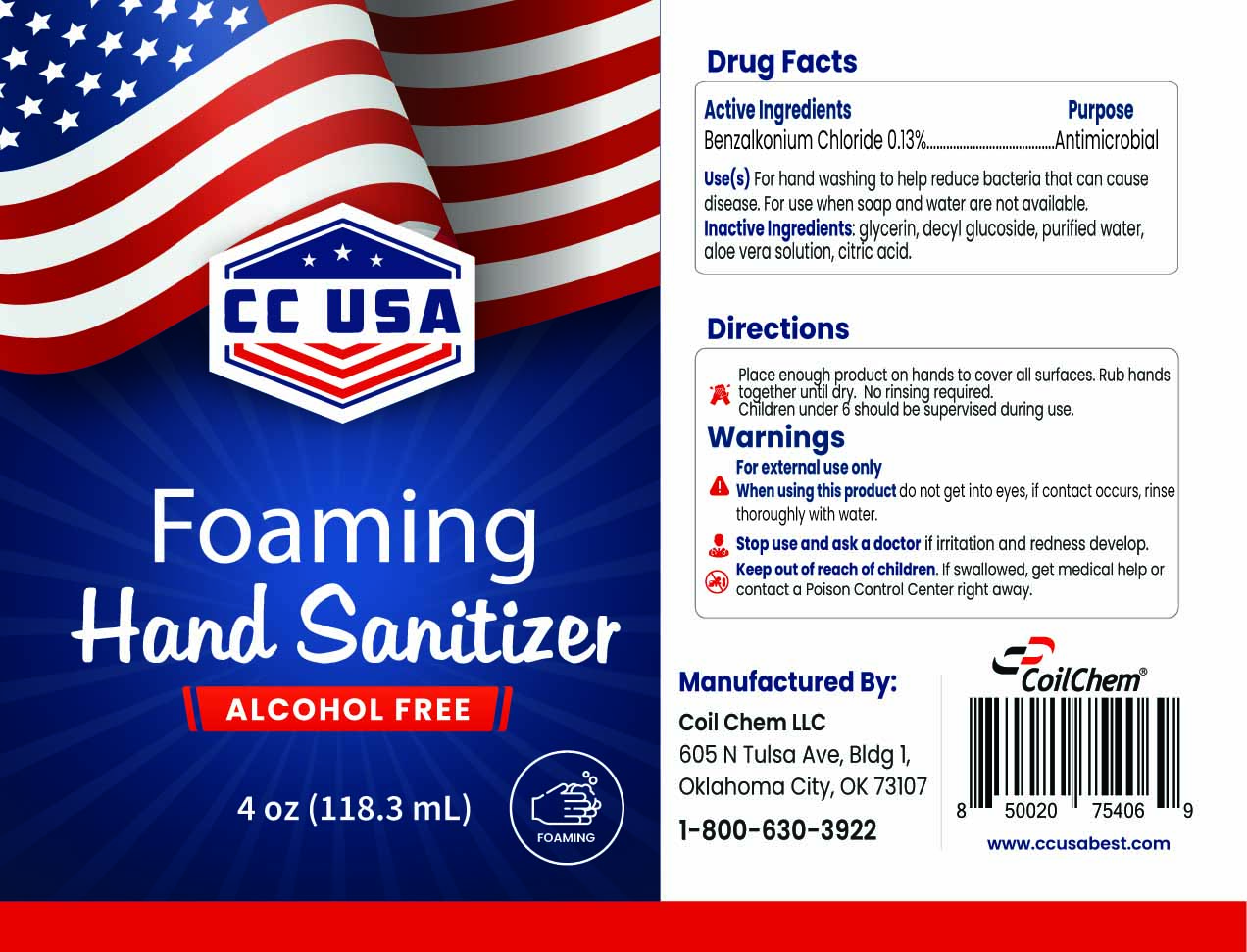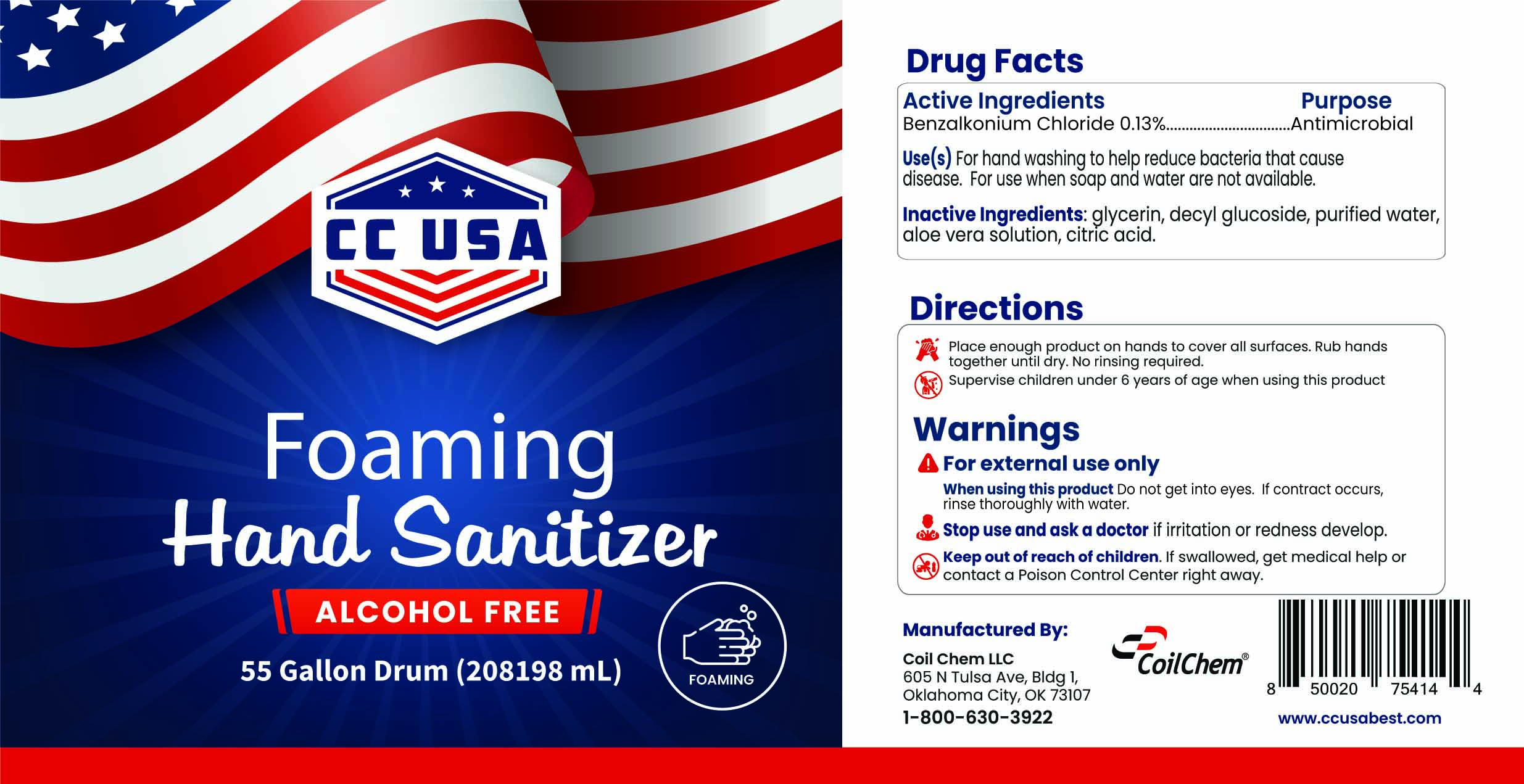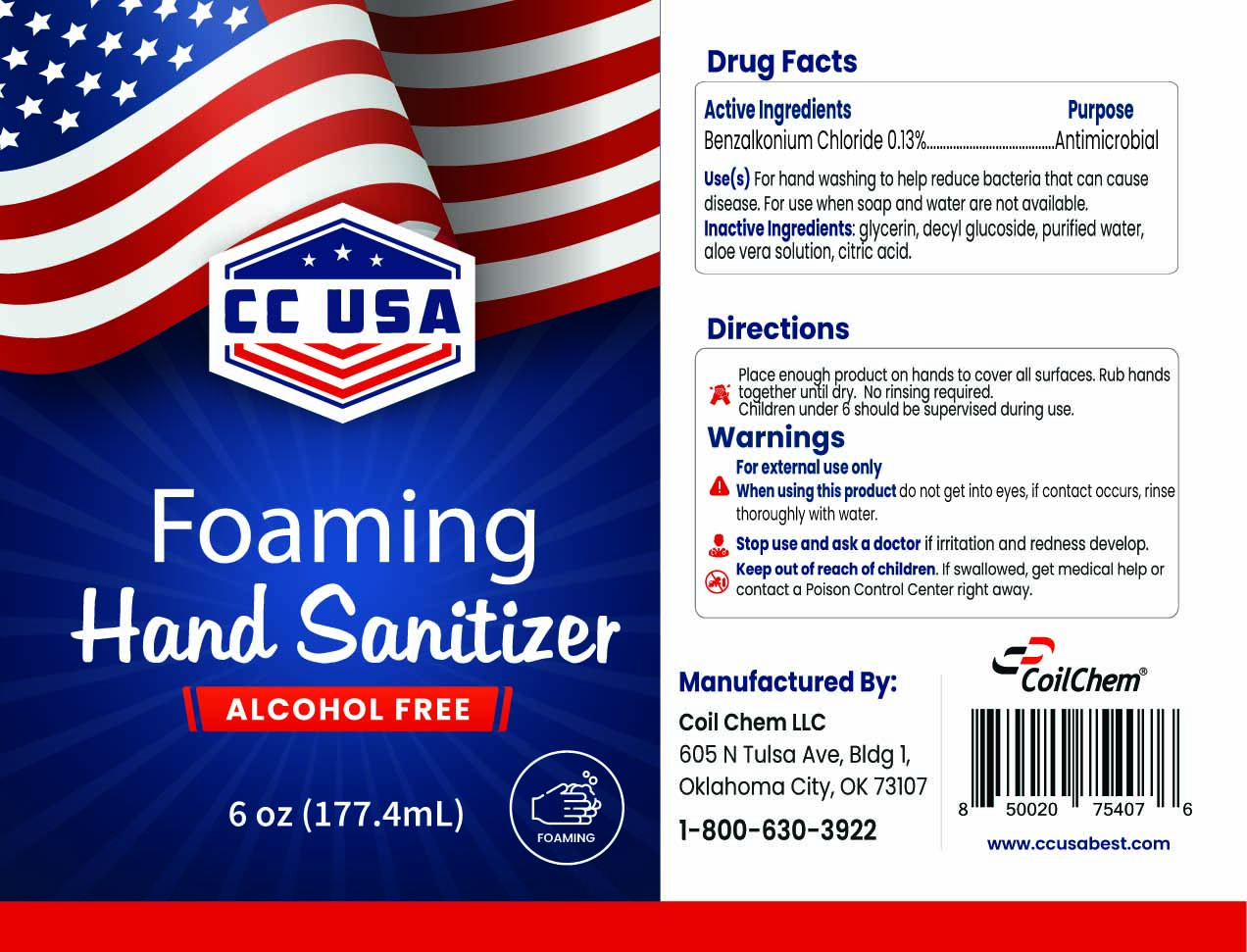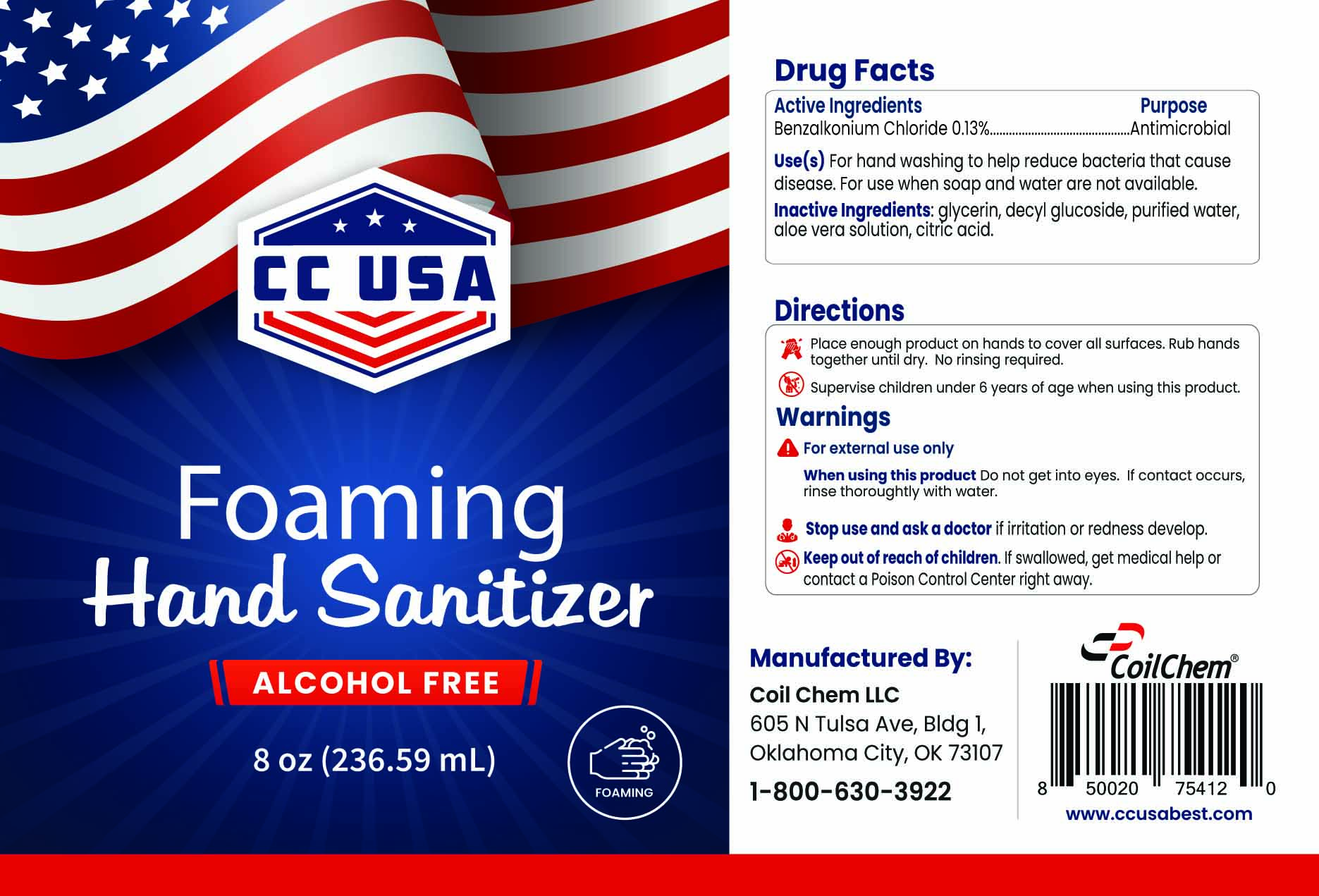 DRUG LABEL: CC USA Non-Alcohol Foaming Hand Sanitizer
NDC: 75508-005 | Form: LIQUID
Manufacturer: Coil Chem LLC
Category: otc | Type: HUMAN OTC DRUG LABEL
Date: 20200917

ACTIVE INGREDIENTS: BENZALKONIUM CHLORIDE 0.13 mg/100 mL
INACTIVE INGREDIENTS: GLYCERIN 2 mL/100 mL; ANHYDROUS CITRIC ACID 0.005 mL/100 mL; ALOE VERA LEAF 0.01 mL/100 mL; WATER 97.355 mL/100 mL; DECYL GLUCOSIDE 0.5 mL/100 mL

Acctive Ingredients

Benzalkonium Chloride 0.13%

Purpose

Antimicrobial

Use(s)

For hand washing to help reduce bacteria that cause disease. For use when soap and water are not available.

Inactive Ingredients:

glycerin, decyl glucoside, purified water, aloe vera solution, citric acid.

Directions

Place enough product on hands to cover all surfaces. Rub hands together until dry. No rinsing required.

Supervise children under 6 years of age when using this product.

Warnings

For external use only

When using this product

Do not get into eyes. If contact offurs, rinse thoroughly with water.

Stop use and ask a doctor

if irritation and redness develop.

Keep out of reach of children.

If swallowed, get medical help or contact a Poison Control Center right away.

Package Label - Principal Display Panel

NDC: 75508-005-01 999349 mL

Package Label - Principal Display Panel

NDC: 75508-005-02 208198 mL

Package Label - Principal Display Panel

NDC: 75508-005-03 3785.41 mL

Package Label - Principla Display Panel

NDC: 75508-005-04 1892.7 mL

Package Label - Principal Display Panel

NDC: 75508-005-05 946.35 mL

Package Label - Principal Display Panel

NDC: 75508-005-06 473.18 mL

Package Label - Principal Display Panel

NDC: 75508-005-07 236.59 mL

Package Label - Principal Display Panel

NDC: 75508-005-08 177.4 mL

Package Label - Principal Display Panel

NDC: 75508-005-09 118.3 mL

Package Label - Principal Display Panel

NDC: 75508-005-10 59.1 mL